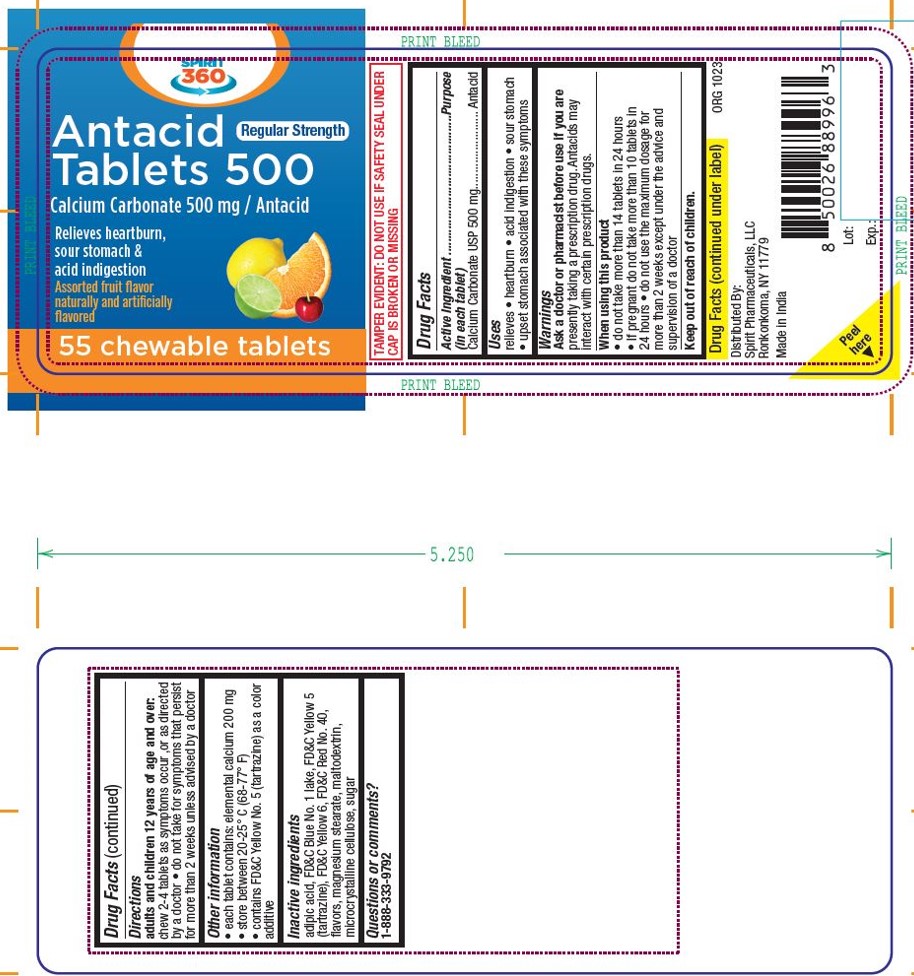 DRUG LABEL: Calcium carbonate
NDC: 68210-5027 | Form: TABLET, CHEWABLE
Manufacturer: Spirit Pharmaceutical LLC
Category: otc | Type: HUMAN OTC DRUG LABEL
Date: 20241230

ACTIVE INGREDIENTS: CALCIUM CARBONATE 500 mg/1 1
INACTIVE INGREDIENTS: ADIPIC ACID; FD&C BLUE NO. 1 ALUMINUM LAKE; FD&C YELLOW NO. 5; FD&C YELLOW NO. 6; FD&C RED NO. 40; MAGNESIUM STEARATE; MALTODEXTRIN; MICROCRYSTALLINE CELLULOSE; SUCROSE

Spirit 360 Antacid Tablets